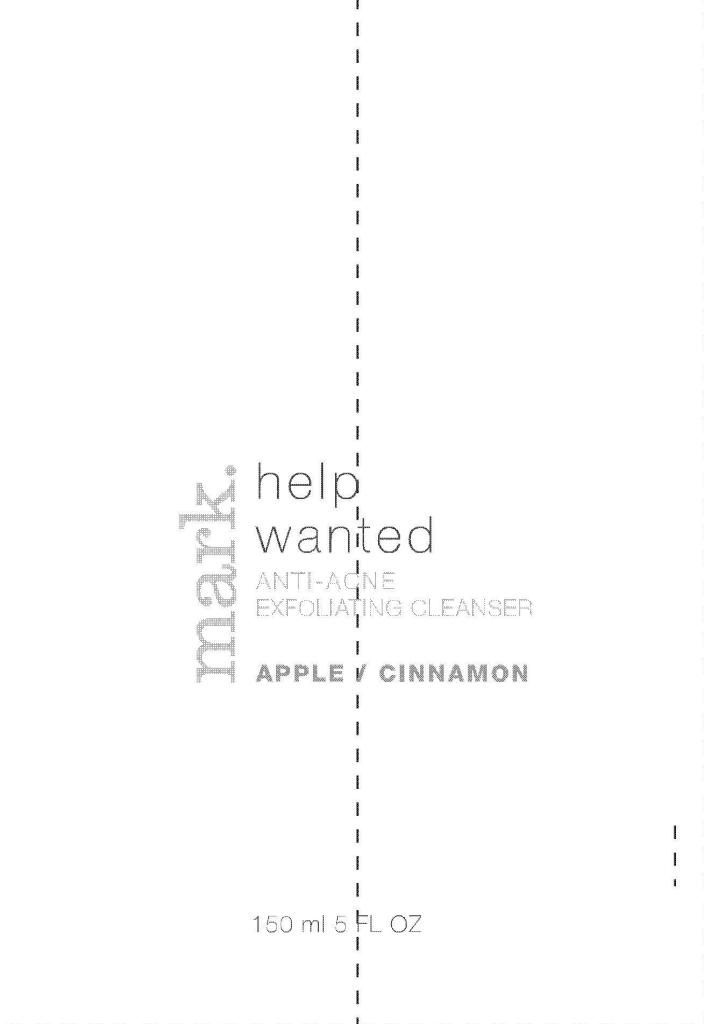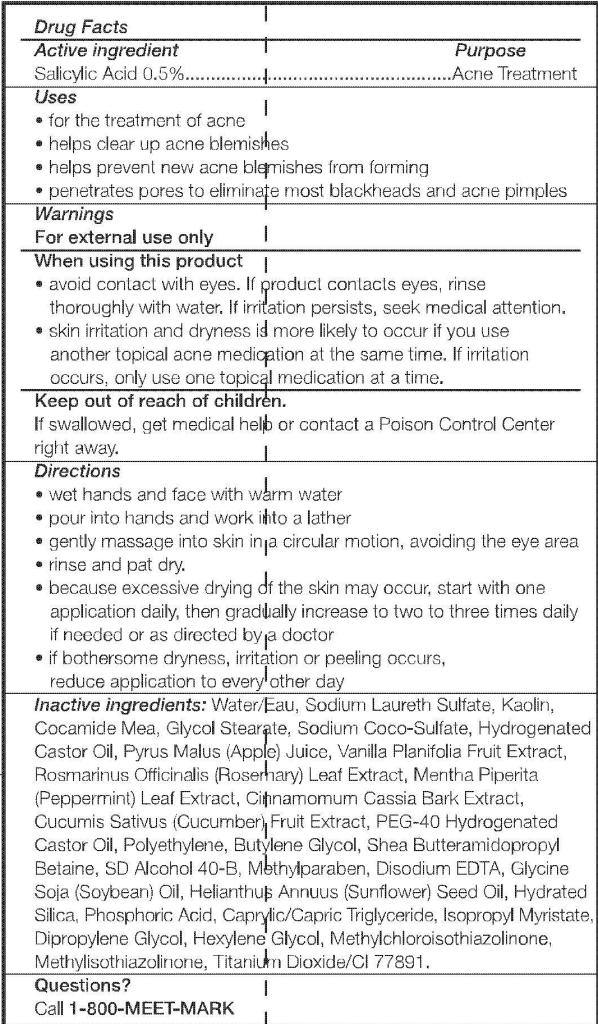 DRUG LABEL: mark. Help Wanted
NDC: 10096-0237 | Form: PASTE
Manufacturer: Avon Products, Inc.
Category: otc | Type: HUMAN OTC DRUG LABEL
Date: 20101220

ACTIVE INGREDIENTS: SALICYLIC ACID	 0.75 mL/150 mL
INACTIVE INGREDIENTS: WATER	; SODIUM LAURETH SULFATE	; KAOLIN	; GLYCOL STEARATE	; HYDROGENATED CASTOR OIL	; BUTYLENE GLYCOL	; METHYLPARABEN	; HYDRATED SILICA	; PHOSPHORIC ACID	; DIPROPYLENE GLYCOL	; HEXYLENE GLYCOL	; METHYLCHLOROISOTHIAZOLINONE	; METHYLISOTHIAZOLINONE	; TITANIUM DIOXIDE	

Drug Facts

Active ingredient

Salicylic Acid 0.5%.................

Purpose

.....................Acne Treatment

Uses

- for the treatment of acne
- helps clear up acne blemishes
- helps prevent new acne blemishes from forming
- penetrates pores to eliminate most blackheads and acne pimples

Warnings
For external use only

When using this product

- avoid contact with eyes. If product contacts eyes, rinse thoroughly with water. If irritation persists, seek medical attention.
- skin irritation and dryness is more likely to occur if you use another topical acne medication at the same time. If irritation occurs, only use one topical medication at a time.

Keep out of reach of children.

If swallowed, get medical help or contact a Poison Control Center right away.

Directions

- wet hands and face with warm water
- pour into hands and work into a lather
- gently massage into skin in a circular motion, avoiding the eye area
- rinse and pat dry.
- because excessive drying of the skin may occur, start with one application daily, then gradually increase to two to three times daily if needed or as directed by a doctor
- if bothersome dryness, irritation or peeling occurs, reduce application to every other day

Inactive ingredients: WATER/EAU
SODIUM LAURETH SULFATE
KAOLIN
COCAMIDE MEA
GLYCOL STEARATE
SODIUM COCO-SULFATE
HYDROGENATED CASTOR OIL
PYRUS MALUS (APPLE) JUICE
VANILLA PLANIFOLIA FRUIT EXTRACT
ROSMARINUS OFFICINALIS (ROSEMARY) LEAF EXTRACT
MENTHA PIPERITA (PEPPERMINT) LEAF EXTRACT
CINNAMOMUM CASSIA BARK EXTRACT
CUCUMIS SATIVUS (CUCUMBER) FRUIT EXTRACT
PEG-40 HYDROGENATED CASTOR OIL
POLYETHYLENE
BUTYLENE GLYCOL
SHEA BUTTERAMIDOPROPYL BETAINE
SD ALCOHOL 40-B
METHYLPARABEN
DISODIUM EDTA
GLYCINE SOJA (SOYBEAN) OIL
HELIANTHUS ANNUUS (SUNFLOWER) SEED OIL
HYDRATED SILICA
PHOSPHORIC ACID
CAPRYLIC/CAPRIC TRIGLYCERIDE
ISOPROPYL MYRISTATE
DIPROPYLENE GLYCOL
HEXYLENE GLYCOL
METHYLCHLOROISOTHIAZOLINONE
METHYLISOTHIAZOLINONE
TITANIUM DIOXIDE/CI 77891

Questions?

Call 1-800-MEET-MARK